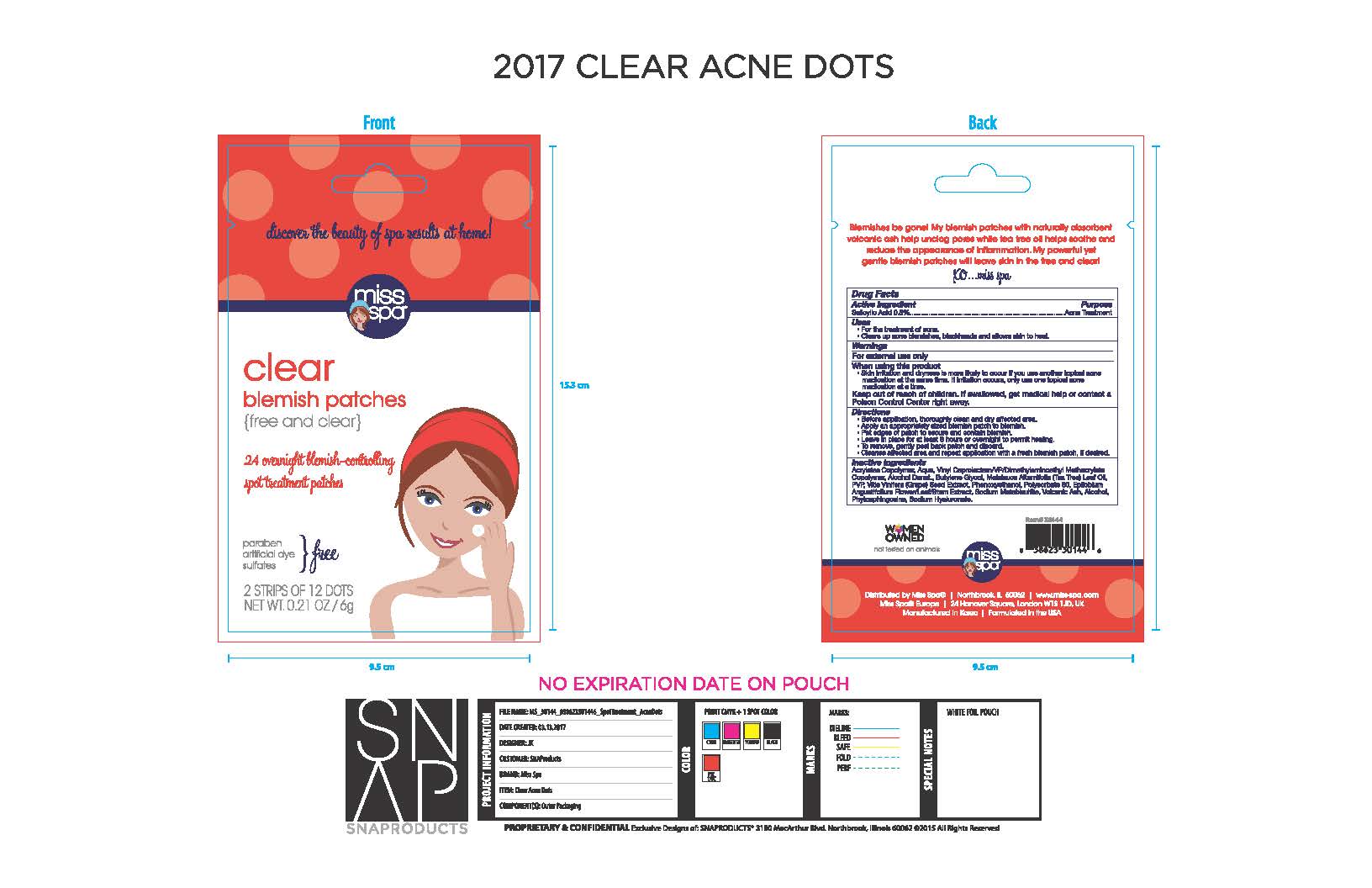 DRUG LABEL: Miss Spa Clear Blemish Patches
NDC: 71420-103 | Form: PATCH
Manufacturer: Sales and Product Solutions
Category: otc | Type: HUMAN OTC DRUG LABEL
Date: 20230310

ACTIVE INGREDIENTS: SALICYLIC ACID 5 g/1 1
INACTIVE INGREDIENTS: BUTYL ACRYLATE/METHYL METHACRYLATE/METHACRYLIC ACID COPOLYMER (18000 MW); STREPTOCOCCUS PYOGENES; ALCOHOL; MELALEUCA ALTERNIFOLIA LEAF; 2-PROPENOIC ACID, 2-(PHOSPHONOOXY)-; PHENOXYETHANOL; WATER; POLYSORBATE 80; POVIDONE, UNSPECIFIED; BUTYLENE GLYCOL; EPILOBIUM ANGUSTIFOLIUM LEAF; VITIS VINIFERA SEED; SODIUM METABISULFITE; PHYTOSPHINGOSINE

Miss Spa Clear Blemish Patches

ACTIVE INGREDIENT

Salicylic Acid 0.5%

PURPOSE

Acne Treatment

INDICATIONS & USAGE

For the treatment of acne

Clears up acne blemishes, blackheads and allows skin to heal.

WARNINGS

For External Use Only.

When using this product

Skin irritation and dryness is more likely to occur if you use another topical acne medication at the same time. If irritation occurs, only use one topical acne medication at a time.

KEEP OUT OF REACH OF CHILDREN

If swallowed, get medical help or contact a Poison Control Center right away

DOSAGE & ADMINISTRATION

Before application, thoroughly clean and dry affected area.
Apply an appropriately sized patch to blemish
Pat edges of patch to secure and contain blemish.
Leave in place for at least 8 hours or overnight to permit healing
To remove, gently peel back patch and discard.
Cleanse affected area and repeat application with a fresh blemish patch, if desired.

INACTIVE INGREDIENT

Acrylates Copolymer, Aqua, Vinyl Caprolactam/VP/dimethylaminoethyl Methacrylate Copolymer, Alcohol Denat. Butylene Glycol, Melaleuca Alternifolia (Tea Tree) Leaf Oil, PVP, Vitis Vinifera (Grape) Seed Extract, Phenoxyethanol, Polysorbate 80, Epilobium Angustifolium Flower/Leaf/Stem Extract, Sodium Metabisulfite, Volcanic Ash, Alcohol, Phytosphingosine, Sodium Hyaluronate